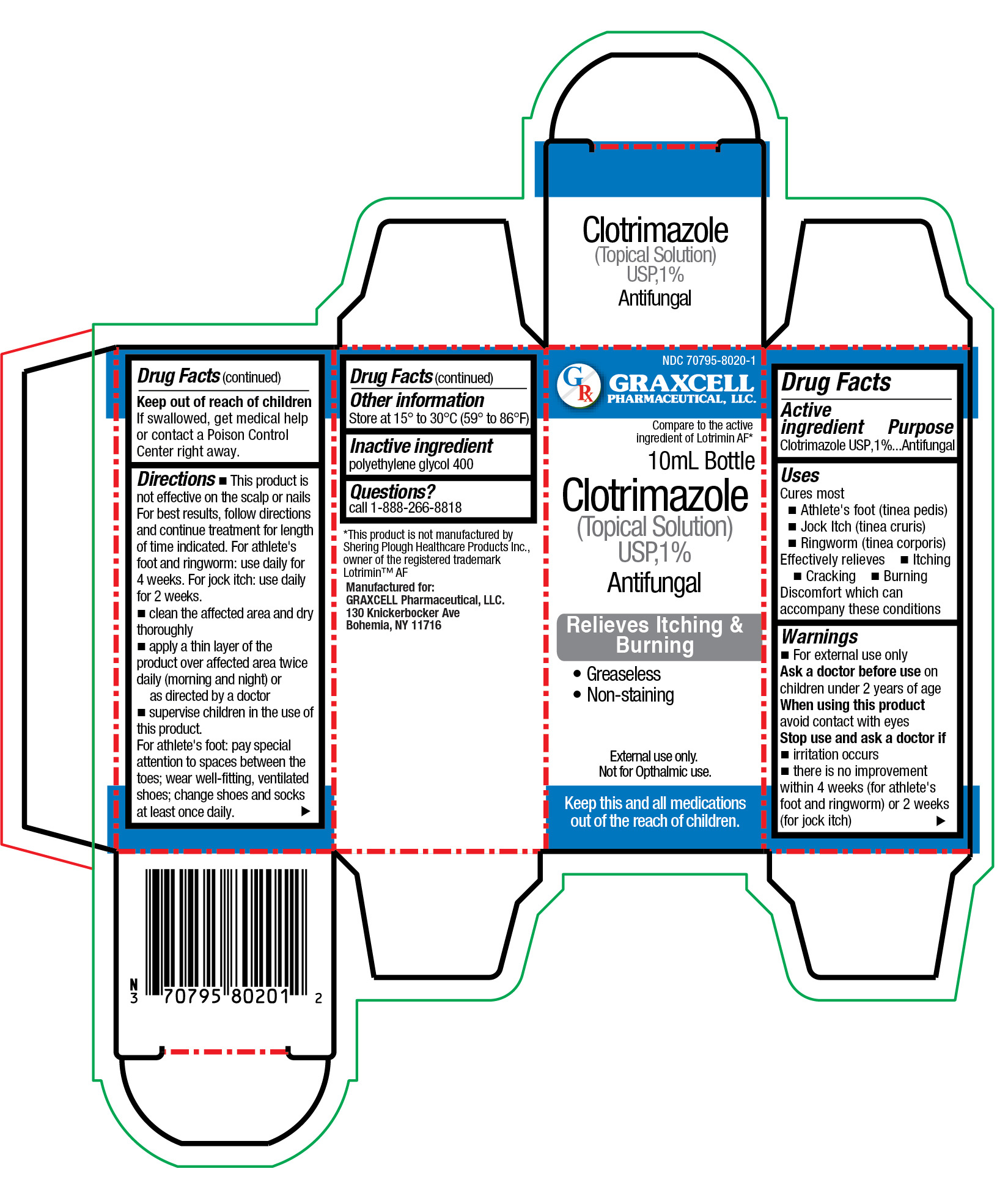 DRUG LABEL: CLOTRIMAZOLE
NDC: 70795-8020 | Form: SOLUTION
Manufacturer: GRAXCELL PHARMACEUTICAL, LLC.
Category: otc | Type: HUMAN OTC DRUG LABEL
Date: 20251225

ACTIVE INGREDIENTS: CLOTRIMAZOLE 1 g/1 mL
INACTIVE INGREDIENTS: POLYETHYLENE GLYCOL 400

CLOTRIMAZOLE (TOPICAL SOLUTION) USP, 1%

ACTIVE INGREDIENT

CLOTRIMAZOLE USP, 1%

PURPOSE

ANTIFUNGAL

USES

Cures most

- Athlete's foot (tinea pedis)
- Jock Itch (tinea cruris)
- Ringworm (tinea corporis)

Effectively relieves

- itching
- cracking
- burning

Discomfort which can accompany these conditions

warnings

- For external use only

Ask a doctor before use

on children under 2 years of age

When using this product

avoid contact with eyes

Stop use and ask a doctorif

- irritation occurs
- there is no improvement within 4 weeks (for athlete's foot and ringworm) or 2 weeks (for jock itch)

KEEP OUT OF REACH OF CHILDREN

If swallowed, get medical help or contact a poison control center right away.

Directions

This product is not effective on the scalp or nails. For best results, follow directions and continue treatment for length of time indicated. For athlete's foot and ringworm: use daily for 4 weeks. For jock itch: use daily for 2 weeks.

- clean the affected area and dry thoroughly
- apply a thin layer of the product over affected area twice daily (morning and night) or as directed by a doctor
- supervise children in the use of this product.

For athlete's foot: pay special attention to spaces between the toes; wear well-fitting, ventilated shoes; change shoes and socks at least once daily.

other information

- Store at 15°to 30°C (59° to 86°F)

inactive ingredients

polyethylene glycol 400

questions?

please call 1-888-266-8818

PRINCIPAL DISPLAY PANEL-10ML BOTTLE CARTON

NDC 70795-8020-1

GRAXCELL PHARMACEUTICAL, LLC.

Compare to the active ingredient of Lotrimin®AF*

10ML Bottle

Clotrimazole (Topical Solution) USP,1%

Antifungal

Relieves Itching & Burning

- Greaseless
- Non-staining

For External use only.
Not for Opthalmic use.

Keep this and all medications out of the reach of children.